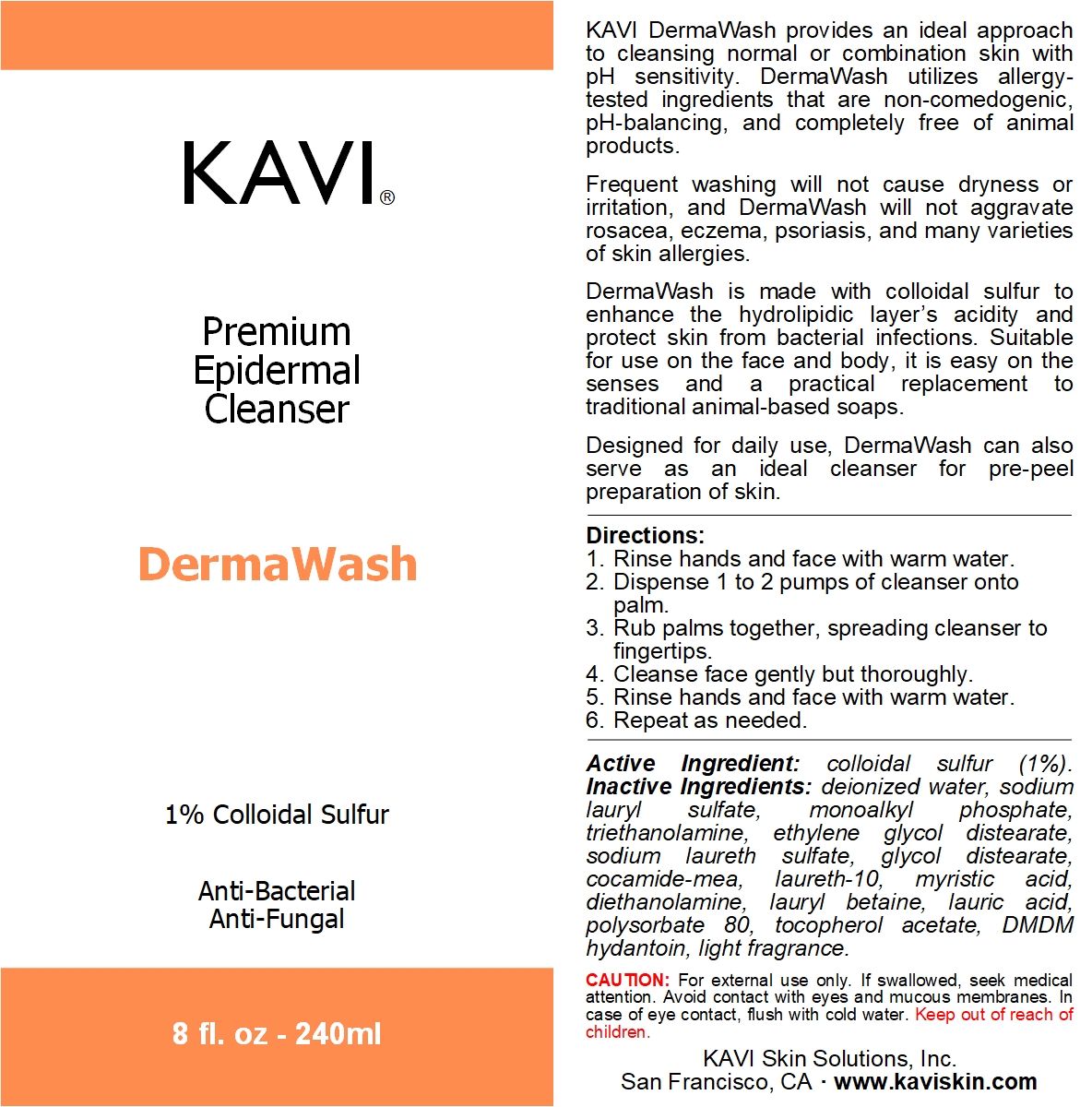 DRUG LABEL: DermaWash
NDC: 42771-0035 | Form: SOAP
Manufacturer: KAVI Skin Solutions, Inc.
Category: otc | Type: HUMAN OTC DRUG LABEL
Date: 20201020

ACTIVE INGREDIENTS: SULFUR 1 g/100 g
INACTIVE INGREDIENTS: TROLAMINE 7 g/100 g; GLYCOL DISTEARATE 3 g/100 g; SODIUM LAURETH SULFATE 3 g/100 g; MYRISTIC ACID 2 g/100 g; LAURYL BETAINE 2 g/100 g; WATER 57.75 g/100 g; SODIUM LAURYL SULFATE 10 g/100 g

DermaWash

Dosage & Administration

Directions for Use:
1. Rinse face and/or body with warm water.
2. Dispense 1 to 2 pumps of cleanser onto palm or washcloth.
3. Rub palms or washcloth together, spreading cleanser evenly and building a lather.
4. Cleanse skin gently but thoroughly.
5. Rinse face and/or body with warm water.

Purpose

KAVI DermaWash provides an ideal approach to cleansing normal or combination skin with pH sensitivity. DermaWash utilizes allergy-tested ingredients that are non-comedogenic, pH-balancing, and completely free of animal products.
Frequent washing will not cause dryness or irritation, and DermaWash will not aggravate rosacea, eczema, psoriasis, and many varieties of skin allergies.
DermaWash is made with colloidal sulfur to enhance the hydrolipidic layer’s acidity and protect skin from bacterial infections. Suitable for use on the face and body, it is easy on the senses and a practical replacement to traditional animal-based soaps.
Designed for daily use, DermaWash can also serve as an ideal cleanser for pre-peel preparation of skin.

Indications & Usage

DermaWash is best suited for the treatment of acne-prone skin.

Directions:
1. Rinse face and/or body with warm water.
2. Dispense 1 to 2 pumps of cleanser onto palm or washcloth.
3. Rub palms or washcloth together, spreading cleanser evenly and building a lather.
4. Cleanse skin gently but thoroughly.
5. Rinse face and/or body with warm water.

Active Ingredients

Active Ingredient: colloidal sulfur (1%)

Inactive Ingredients

Inactive Ingredients: deionized water, sodium lauryl sulfate, monoalkyl phosphate, triethanolamine, ethylene glycol distearate, sodium laureth sulfate, glycol distearate, cocamide-mea, laureth-10, myristic acid, diethanolamine, lauryl betaine, lauric acid, polysorbate 80, tocopherol acetate, DMDM hydantoin, light fragrance.

Warnings

For external use only. If swallowed, seek medical attention. Avoid contact with eyes and mucous membranes. In case of eye contact, flush with cold water. Keep out of reach of children.

Keep out of reach of children

CAUTION: For external use only. If swallowed, seek medical attention. Avoid contact with eyes and mucous membranes. In case of eye contact, flush with cold water. Keep out of reach of children.

Front and Back Labels

KAVI DermaWash provides an ideal approach to cleansing normal or combination skin with pH sensitivity. DermaWash utilizes allergy-tested ingredients that are non-comedogenic, pH-balancing, and completely free of animal products.
Frequent washing will not cause dryness or irritation, and DermaWash will not aggravate rosacea, eczema, psoriasis, and many varieties of skin allergies.
DermaWash is made with colloidal sulfur to enhance the hydrolipidic layer’s acidity and protect skin from bacterial infections. Suitable for use on the face and body, it is easy on the senses and a practical replacement to traditional animal-based soaps.
Designed for daily use, DermaWash can also serve as an ideal cleanser for pre-peel preparation of skin.

Directions:
1. Rinse hands and face with warm water.
2. Dispense 1 to 2 pumps of cleanser onto palm.
3. Rub palms together, spreading cleanser to fingertips.
4. Cleanse face gently but thoroughly.
5. Rinse hands and face with warm water.
6. Repeat as needed.

Active Ingredient: colloidal sulfur (1%). Inactive Ingredients: deionized water, sodium lauryl sulfate, monoalkyl phosphate, triethanolamine, ethylene glycol distearate, sodium laureth sulfate, glycol distearate, cocamide-mea, laureth-10, myristic acid, diethanolamine, lauryl betaine, lauric acid, polysorbate 80, tocopherol acetate, DMDM hydantoin, light fragrance.

CAUTION: For external use only. If swallowed, seek medical attention. Avoid contact with eyes and mucous membranes. In case of eye contact, flush with cold water. Keep out of reach of children.

KAVI Skin Solutions, Inc.
San Francisco, CA · www.kaviskin.com